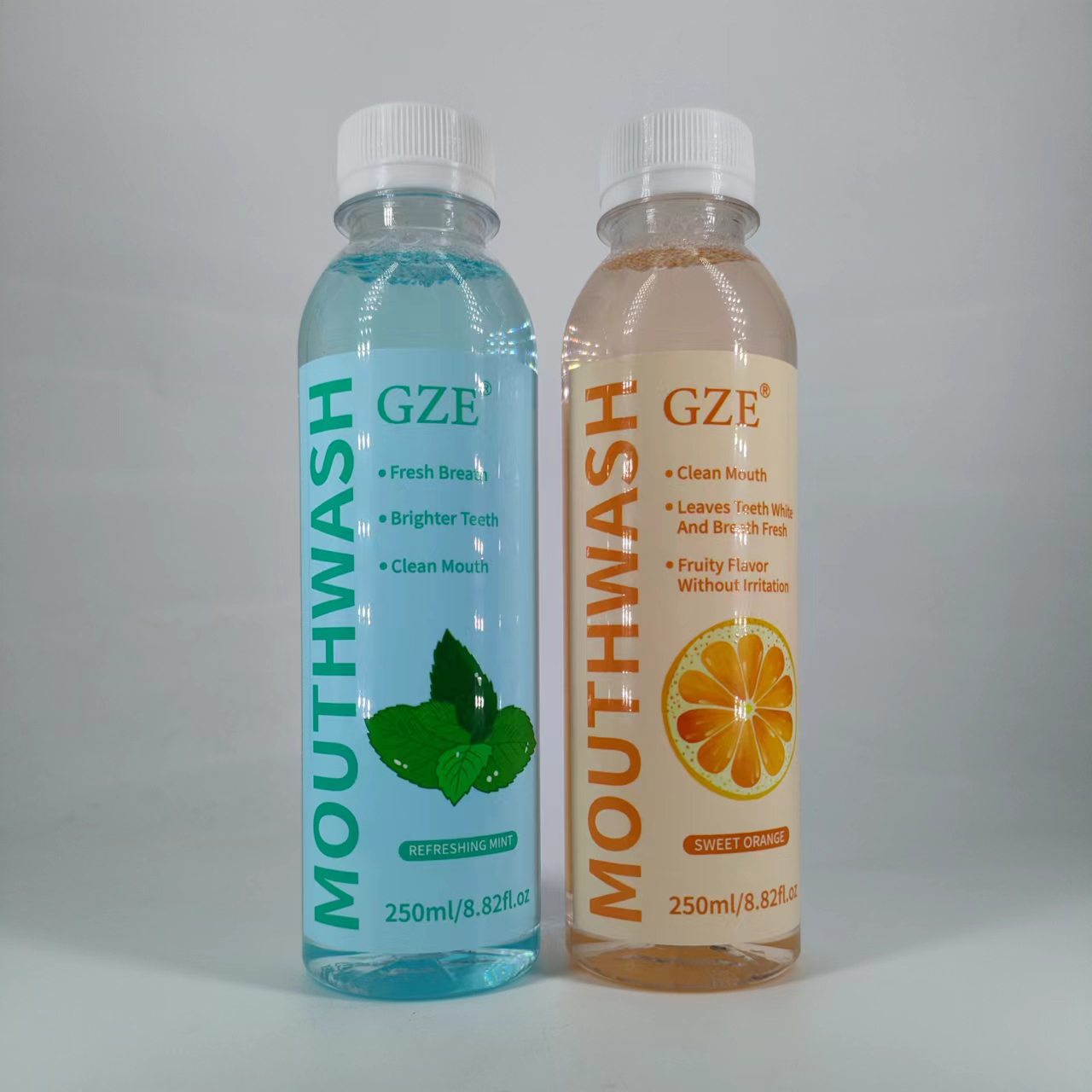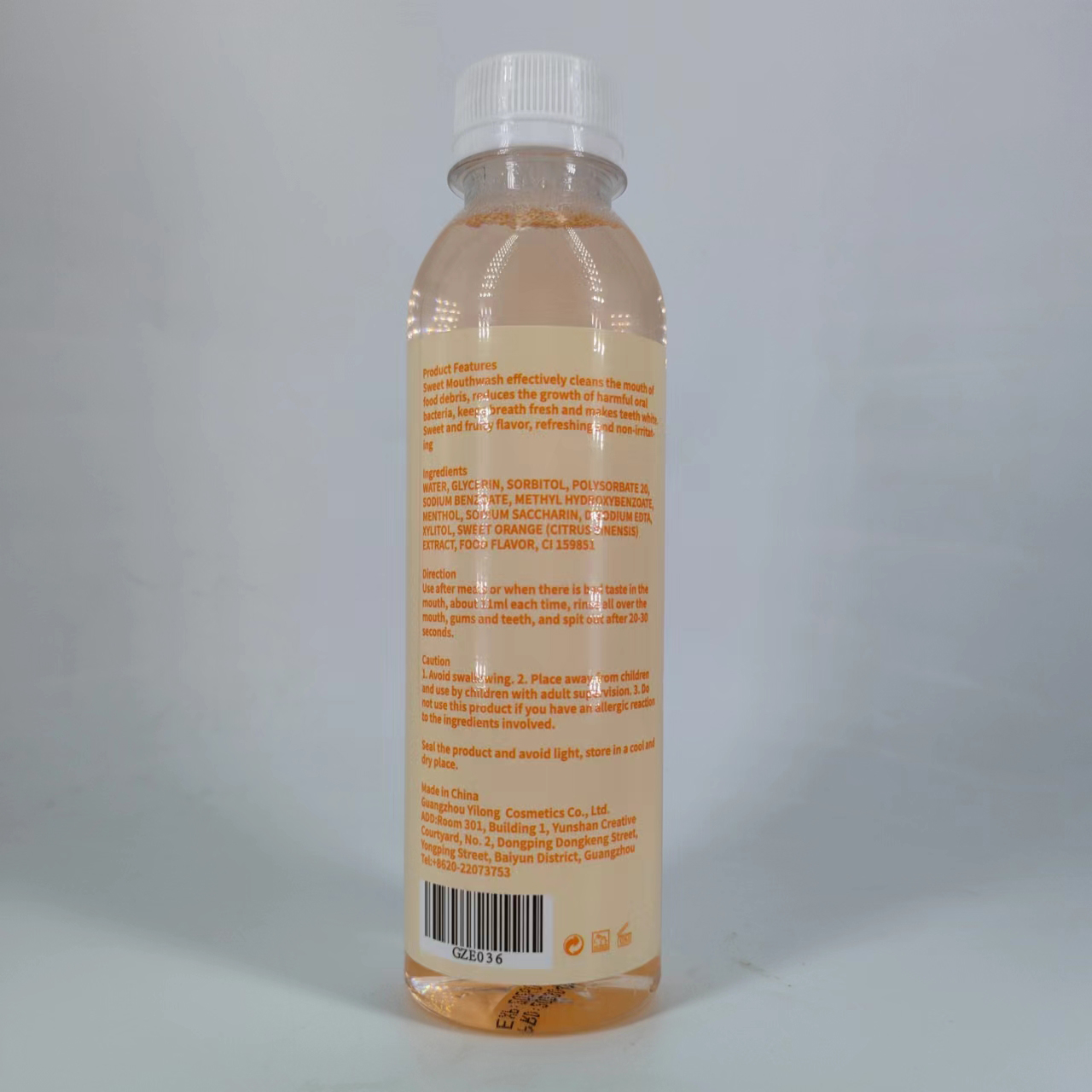 DRUG LABEL: GZE  Mouthwash
NDC: 83566-035 | Form: LIQUID
Manufacturer: Guangzhou Yilong Cosmetics Co.,Ltd.
Category: otc | Type: HUMAN OTC DRUG LABEL
Date: 20240604

ACTIVE INGREDIENTS: MENTHOL 2 g/100 mL; ORANGE OIL 2 g/100 mL; XYLITOL 2 g/100 mL
INACTIVE INGREDIENTS: DISODIUM EDTA-COPPER; GLYCERIN; SORBITOL; SODIUM BENZOATE; WATER; POLYSORBATE 20; METHYLPARABEN SODIUM

GZE MOUTHWASH

ACTIVE INGREDIENT

Menthol
Xylitol

Citrus Aurantium Dulcis (Orange) Fruit Extract

INACTIVE INGREDIENT

DISODIUM EDTA-COPPER
DISODIUM EDTA-COPPER
GLYCERIN
SORBITOL
SODIUM BENZOATE
WATER
POLYSORBATE 20
METHYLPARABEN SODIUM

Flavor

CI 15985

INDICATIONS AND USAGE

Use after meals or when there is bad taste in the mouth, about 11ml each time, rinse all over the mouth, gums and teeth, and spit out after 20-30 seconds.

PURPOSE

Sweet Mouthwash effectively cleans the mouth of food debris, reduces the growth of harmful oral bacteria, keeps breath fresh and makes teeth white. Sweet and fruity flavor, refreshing and non-iritating.

WARNINGS

No swallowing

Stop use and ask a doctor if rash occurs.

Do not use on damaged or broken skin.

When using this product keep out of eyes. Rinse with water to remove.

Keep out of reach of children. If swallowed, get medical help or contact a Poison Control Center right away.

DOSAGE AND ADMINISTRATION

Use after meals or when there is bad taste in the mouth, about 11ml each time, rinse all over the mouth, gums and teeth, and spit out after 20-30 seconds.